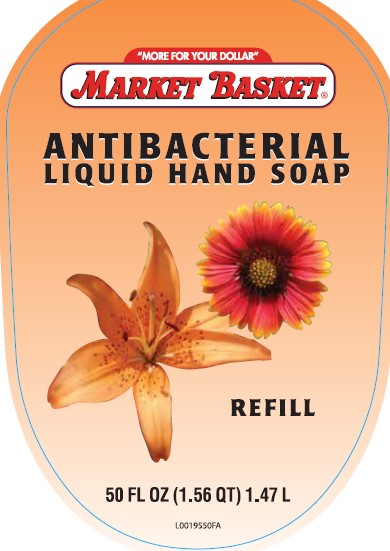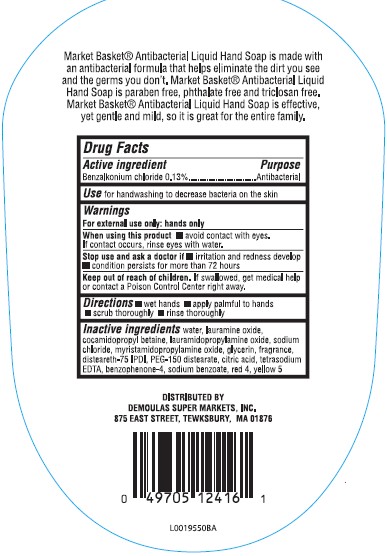 DRUG LABEL: Hand wash
NDC: 53942-403 | Form: LIQUID
Manufacturer: Demoulas Super Markets, Inc
Category: otc | Type: HUMAN OTC DRUG LABEL
Date: 20250331

ACTIVE INGREDIENTS: BENZALKONIUM CHLORIDE 1.3 mg/1 mL
INACTIVE INGREDIENTS: WATER; LAURAMINE OXIDE; COCAMIDOPROPYL BETAINE; LAURAMIDOPROPYLAMINE OXIDE; SODIUM CHLORIDE; MYRISTAMIDOPROPYLAMINE OXIDE; GLYCERIN; DISTEARETH-75 ISOPHORONE DIISOCYANATE; PEG-150 DISTEARATE; CITRIC ACID MONOHYDRATE; EDETATE SODIUM; SULISOBENZONE; SODIUM BENZOATE; FD&C RED NO. 4; FD&C YELLOW NO. 5

Market Basket 403.002/403AC
Amber Antibacterial Hand Soap

Claims

Market Basket®Antibacterial Liquid Hand Soap is made with an antibacterial formula that helps eliminate the dirt you see and the germs you don't. Market Basket®Antibacterial Liquid Hand Soap is paraben free, phthalate free and triclosan free. Market Basket®Antibacterial Liquid Hand Soap is effective, yet gentle and mild, so it is great for the entire family.

Active ingredient

Benzalkonium chloride 0.13%

Purpose

Antibacterial

Use

for handwashing to decrease bacteria on the skin

Warnings

For external use only: hands only

When using this product

- avoid contact with eyes. If contact occurs, rinse eyes thoroughly with water.

Stop use and ask a doctor if

- irritation and redness develop
- condition persists for more than 72 hours

Keep out of reach of children.

If swallowed, get medical help or contact a Poison Control Center right away.

Directions

- wet hands
- apply palmful to hands
- scrub thoroughly
- rinse thoroughly

Inactive ingredients

water, lauramine oxide, cocamidopropyl betaine, lauramidopropylamine oxide, sodium chloride, myristamidopropylamine oxide, glycerin, fragrance, disteareth-75 IPDI, PEG-150 distearate, citric acid, tetrasodium EDTA, benzophenone-4, sodium benzoate, red 4, yellow 5

Adverse reactions

DISTRIBUTED BY

DEMOLAS SUPER MARKETS, INC.

875 EAST STREET, TEWKSBURY, MA 01876

Prncipal display panel

"MORE FOR YOUR DOLLAR"

MARKET BASKET®

ANTIBACTERIAL

LIQUID HAND SOAP

REFILL

50 FL OZ (1.56 QT) 1.47 L